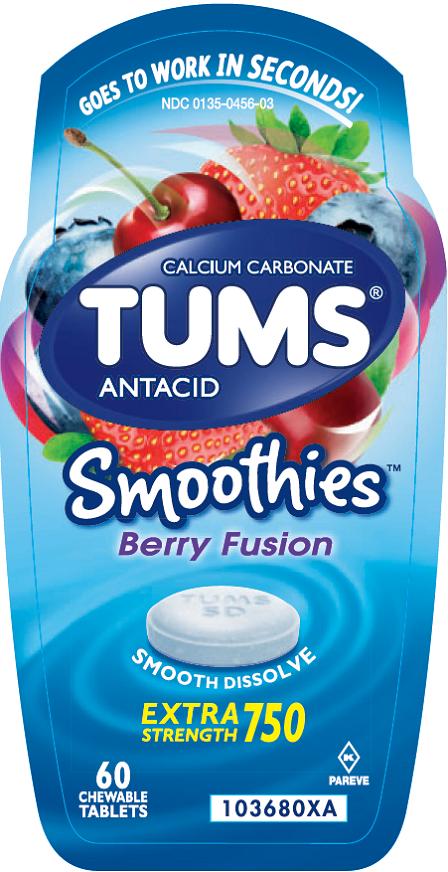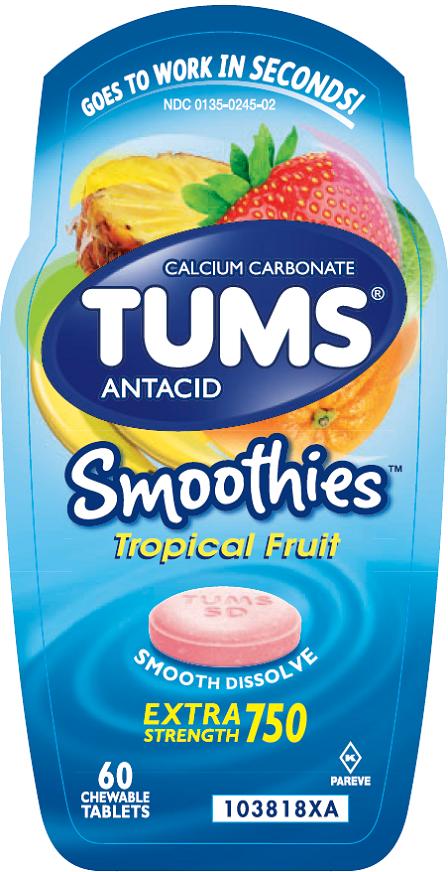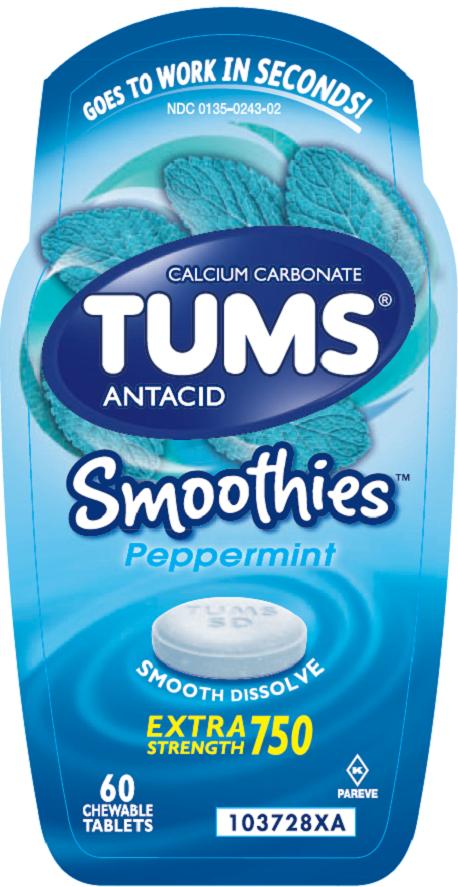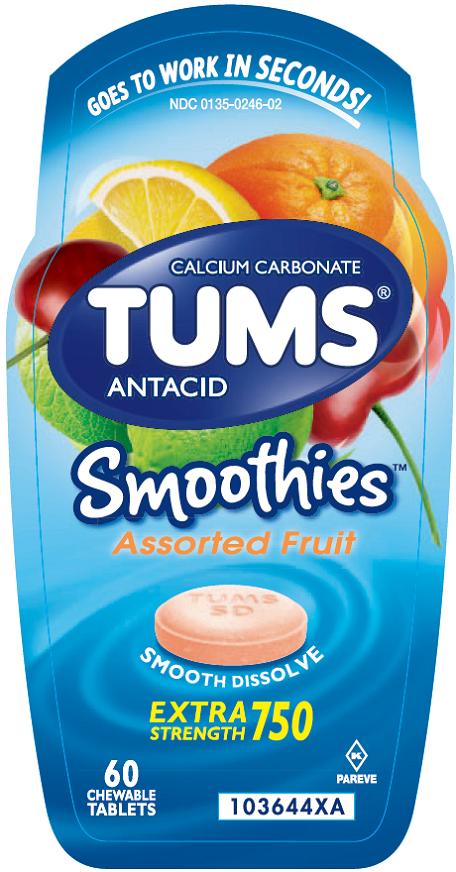 DRUG LABEL: TUMS
NDC: 67296-1256 | Form: TABLET, CHEWABLE
Manufacturer: RedPharm Drug
Category: otc | Type: HUMAN OTC DRUG LABEL
Date: 20240715

ACTIVE INGREDIENTS: CALCIUM CARBONATE 750 mg/1 1
INACTIVE INGREDIENTS: ADIPIC ACID; STARCH, CORN; DEXTROSE, UNSPECIFIED FORM; FD&C BLUE NO. 1; ALUMINUM OXIDE; FD&C RED NO. 40; FD&C YELLOW NO. 5; FD&C YELLOW NO. 6; GUAR GUM; MAGNESIUM STEARATE; MALTODEXTRIN; MICROCRYSTALLINE CELLULOSE; SORBITOL; SUCROSE

Drug Facts

Active ingredient (per tablet)

Calcium Carbonate USP 750 mg

Purpose

Antacid

Uses

relieves

- heartburn
- acid indigestion
- sour stomach
- upset stomach associated with these symptoms

Warnings

Ask a doctor or pharmacist before use if you are

presently taking a prescription drug. Antacids may interact with certain prescription drugs.

When using this product

- do not take more than 10 tablets in 24 hours
- if pregnant do not take more than 6 tablets in 24 hours
- do not use the maximum dosage for more than 2 weeks except under the advice and supervision of a doctor

Directions

- adults and children 12 years of age and over:chew 2 – 4 tablets as symptoms occur, or as directed by a doctor
- do not take for symptoms that persist for more than 2 weeks unless advised by a doctor

Other information

- each tablet contains:elemental calcium 300mg
- store below 25oC (77oF). Keep the container tightly closed.

Inactive ingredients (Assorted Fruit)

adipic acid, corn starch, dextrose, FD&C blue #1 lake, FD&C red #40 lake, FD&C yellow #5 (tartrazine) lake, FD&C yellow #6 lake, flavors, guar gum, magnesium stearate, maltodextrin, microcrystalline cellulose, sorbitol, sucrose

Contains: soy

Inactive ingredients (Berry Fusion)

adipic acid, corn starch, dextrose, FD&C blue #1 lake, FD&C red #40 lake, flavors, guar gum, magnesium stearate, maltodextrin, microcrystalline cellulose, sorbitol, sucrose

Contains: soy

Inactive ingredient (Assorted Tropical Fruit)

adipic acid, corn starch, dextrose, FD&C blue #1 lake, FD&C red #40 lake, FD&C yellow #6 lake, flavors, guar gum, magnesium stearate, maltodextrin, microcrystalline cellulose, sorbitol, sucrose

Contains: soy

Inactive ingredients (Peppermint)

corn starch, dextrose, flavors, guar gum, magnesium stearate, maltodextrin, microcrystalline cellulose, sorbitol, sucrose

Questions?

1-800-897-7535weekdays

Principal Display Panel

NDC 0135-0246-02

TUMS®

CALCIUM CARBONATE

ANTACID

SmoothiesTM

Assorted Fruit

SMOOTH DISSOLVE

EXTRA STRENGTH 750

GOES TO WORK IN SECONDS!

60CHEWABLE TABLETS

PAREVE

©2014 GSK

Safety sealed – Do not use if printed inner seal beneath cap is missing or broken.

GlaxoSmithKline

Moon Twp, PA 15108

Gluten-Free

www.tums.com

Front Panel 103644XA

Back Panel 103553XA

Principal Display Panel

NDC 0135-0456-03

TUMS®

CALCIUM CARBONATE

ANTACID

SmoothiesTM

Berry Fusion

SMOOTH DISSOLVE

EXTRA STRENGTH 750

GOES TO WORK IN SECONDS!

60CHEWABLE TABLETS

PAREVE

Safety sealed – Do not use if printed inner seal beneath cap is missing or broken.

GSKCH

Warren, NJ 07059

Gluten-Free

©2014 GSK

Front Panel 103680XA

Back Panel 103725XA

Principal Display Panel

NDC 0135-0245-02

TUMS®

CALCIUM CARBONATE

ANTACID

SmoothiesTM

Tropical Fruit

SMOOTH DISSOLVE

EXTRA STRENGTH 750

GOES TO WORK IN SECONDS!

60CHEWABLE TABLETS

PAREVE

©2014 GSK

Safety sealed – Do not use if printed inner seal beneath cap is missing or broken.

GlaxoSmithKline

Moon Twp, PA 15108

Gluten-Free

www.tums.com

Front Panel 103818XA

Back Panel 103816XA

Principal Display Panel

NDC 0135-0243-02

TUMS®

CALCIUM CARBONATE

ANTACID

SmoothiesTM

Peppermint

SMOOTH DISSOLVE

EXTRA STRENGTH 750

GOES TO WORK IN SECONDS!

60CHEWABLE TABLETS

PAREVE

Safety sealed – Do not use if printed inner seal beneath cap is missing or broken.

Trademarks are owned by or licensed to the GSK group of companies.

GSKConsumer Healthcare

Warren, NJ 07059

Gluten-Free

©2015 GSK or its licensor.

Front Panel 103728XB

Back Panel 103727XB